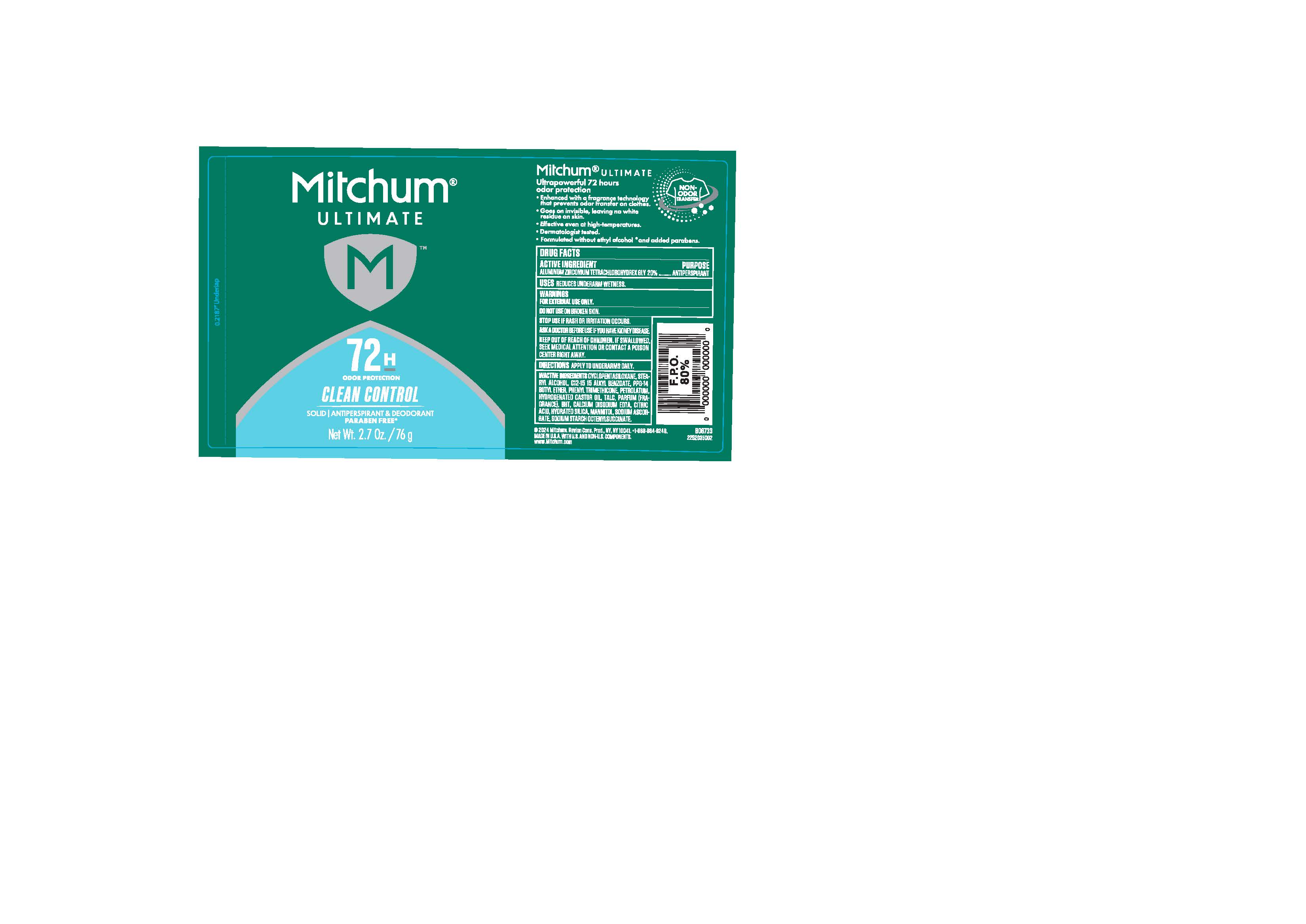 DRUG LABEL: Mitchum Ultimate- 72 hour protection - Clean Control - APDEO
NDC: 10967-791 | Form: STICK
Manufacturer: Revlon Consumer Products Corp.
Category: otc | Type: HUMAN OTC DRUG LABEL
Date: 20250616

ACTIVE INGREDIENTS: ALUMINUM ZIRCONIUM TETRACHLOROHYDREX GLY 15.3653 g/76 g
INACTIVE INGREDIENTS: PPG-14 BUTYL ETHER; PETROLATUM; CALCIUM DISODIUM EDTA; MODIFIED CORN STARCH (1-OCTENYL SUCCINIC ANHYDRIDE); STEARYL ALCOHOL; PHENYL TRIMETHICONE; HYDRATED SILICA; MANNITOL; CYCLOPENTASILOXANE; C12-15 ALKYL BENZOATE; CITRIC ACID; TALC; BHT; HYDROGENATED CASTOR OIL; SODIUM ASCORBATE

Mitchum Ultimate - 72 hour protection - Clean Control - APDEO

Active Ingredient

Aluminum Zirconium Tetrachlorohydrex GLY 20%

Purpose

Antiperspirant

Uses

Reduces underam wetness

Warnings

For external use only.

Do not use on broken skin.

Stop Use

Stop use if rash or irritation occurs.

Ask a doctor before use if you have kidney disease.

Keep out of reach of children, if swallowed, seek medical attention or conduct a poison center right away.

Directions

Directions Apply to underarms only.

Inactive ingredients

Cyclopentasiloxane, Stearyl Alcohol, C12-15 Alkyl Benzoate, PPG-14 Butyl Ether, Phenyl Trimethicone, Petrolatum, Hydrogenated Castor Oil, Parfum (Fragrance), Talc, BHT, Calcium Disodium EDTA, Citric Acid, Hydrated Silica, Mannitol, Sodium Ascorbate, Sodium Starch Octenylsuccinate